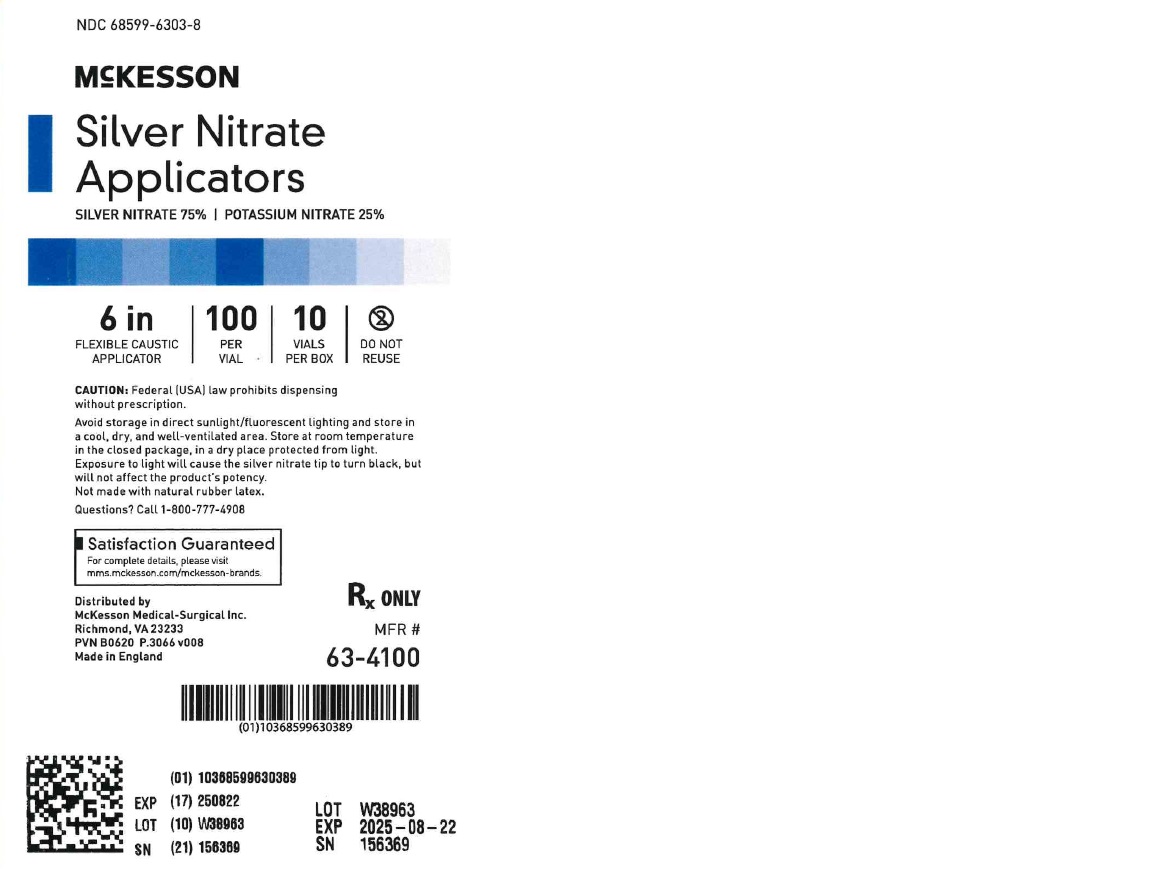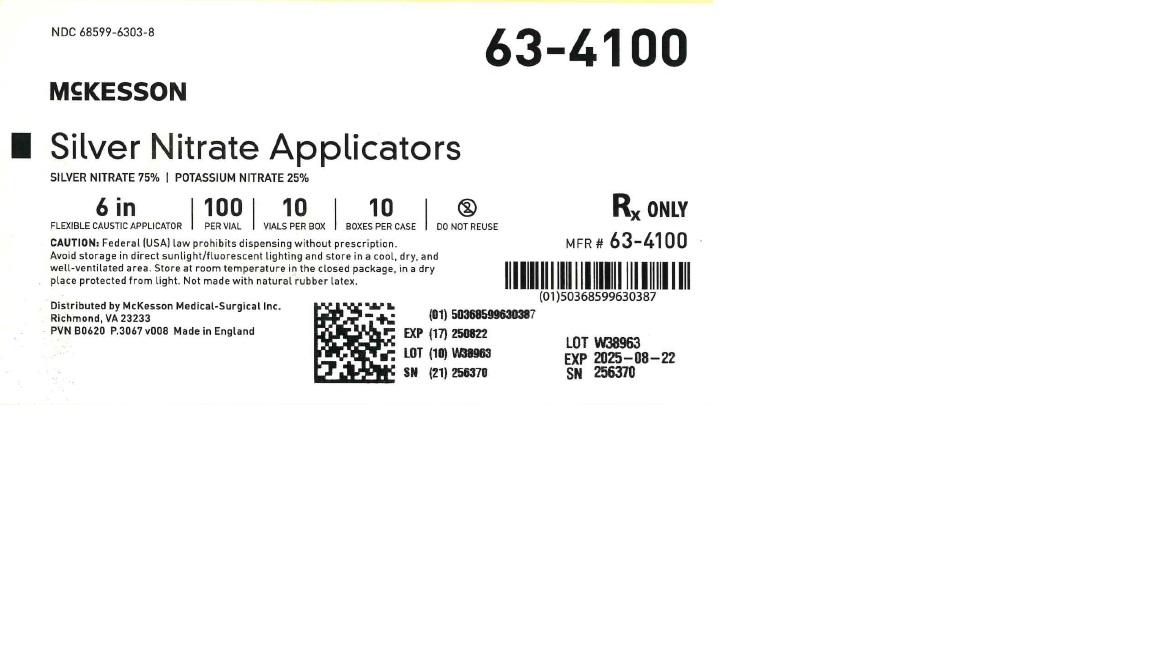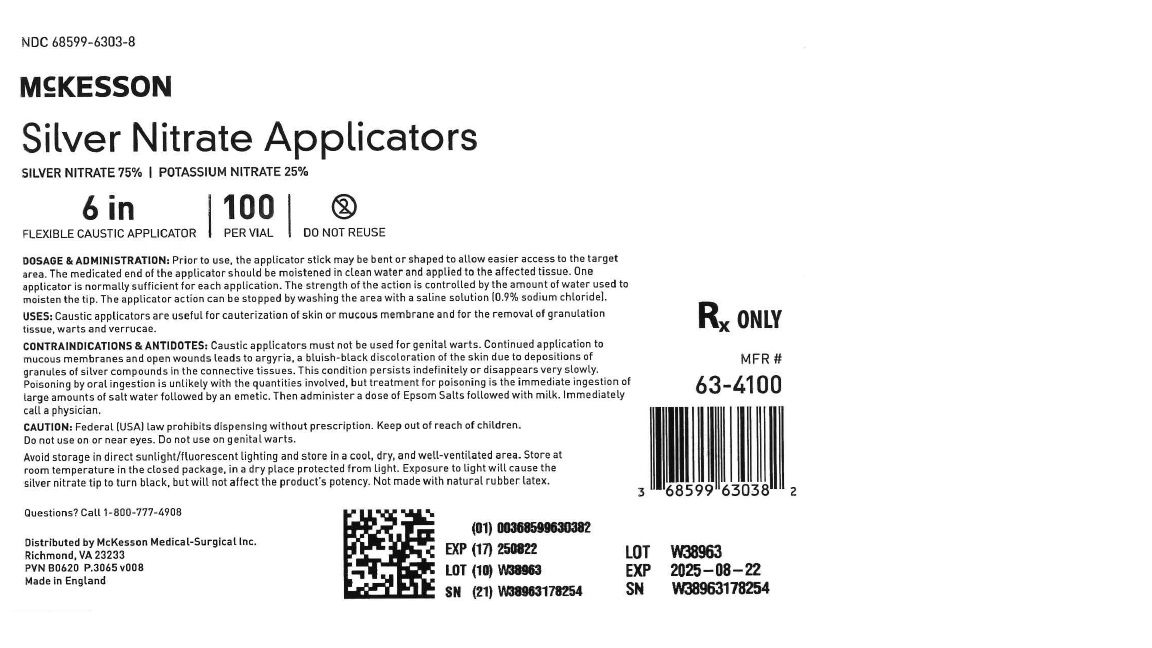 DRUG LABEL: Swabs
NDC: 68599-6303 | Form: SWAB
Manufacturer: McKesson
Category: prescription | Type: HUMAN PRESCRIPTION DRUG LABEL
Date: 20241217

ACTIVE INGREDIENTS: POTASSIUM NITRATE 25 g/100 mL; SILVER NITRATE 75 g/100 mL

Silver Nitrate

Drug Facts

DOSAGE & ADMINISTRATION:
Prior to use, the applicator stick may be bent or shaped to allow easier access to the target area. The
medicated end of the applicator should be moistened in clean water and applied to the affected tissue.
One applicator is normally sufficient for each application. The strength of the action is controlled by
the amount of water used to moisten the tip. The applicator action can be stopped by washing the area
with a saline solution (0.9% sodium chloride).

USES:
Caustic applicators are useful for cauterization of skin or mucous membrane and for the removal of
granulation tissue, warts and verrucae.

CONTRAINDICATIONS & ANTIDOTES:
Caustic applicators must not be used for genital warts. Continued application to mucous membranes and
open wounds leads to argyria, a bluish-black discoloration of the skin due to depositions of granules of
silver compounds in the connective tissues.
This condition persists indefinitely or disappears very slowly. Poisoning by oral ingestion is unlikely
with the quantities involved, but treatment for poisoning is the immediate ingestion of large amounts of
salt water followed by an emetic. Then administer a dose of Epsom Salts followed with milk.
Immediately call a physician.

CAUTION:
Federal (USA) law prohibits dispensing without prescription.

WARNINGS AND PRECAUTIONS

CAUTION:
Federal (USA) law prohibits dispensing without prescription.

Keep out of reach of children.
Do not use on or near eyes. Do not use on genital warts.
Avoid storage in direct sunlight/fluorescent lighting and store in a cool, dry, and well-ventilated area.
Store at room temperature in the closed package, in a dry place protected from light. Exposure to light
will cause the silver nitrate tip to turn black, but will not affect the product's potency.
Not made with natural rubber latex.

Questions?Call 1-800-777-4908

Distributed by McKesson Medical-Surgical Inc.
Richmond, VA 23233

PACKAGE LABEL

NDC 68599-6303-8
McKESSON
Silver Nitrate Applicators
SILVER NITRATE 75% | POTASSIUM NITRATE 25%
6 in
FLEXIBLE CAUSTIC APPLICATOR
100 PER VIAL
10 VIALS PER BOX
DO NOT REUSE
Rx ONLY
MFR # 63-4100